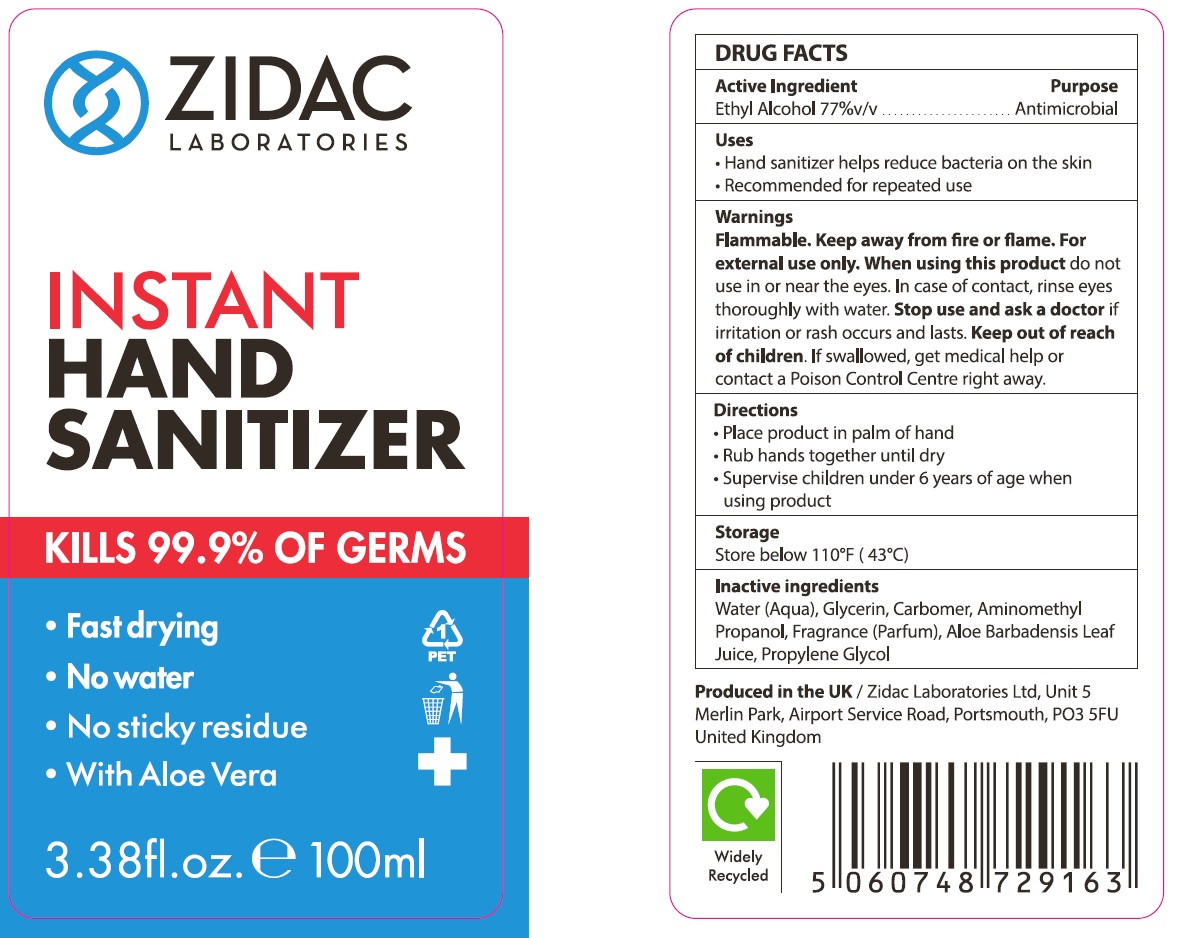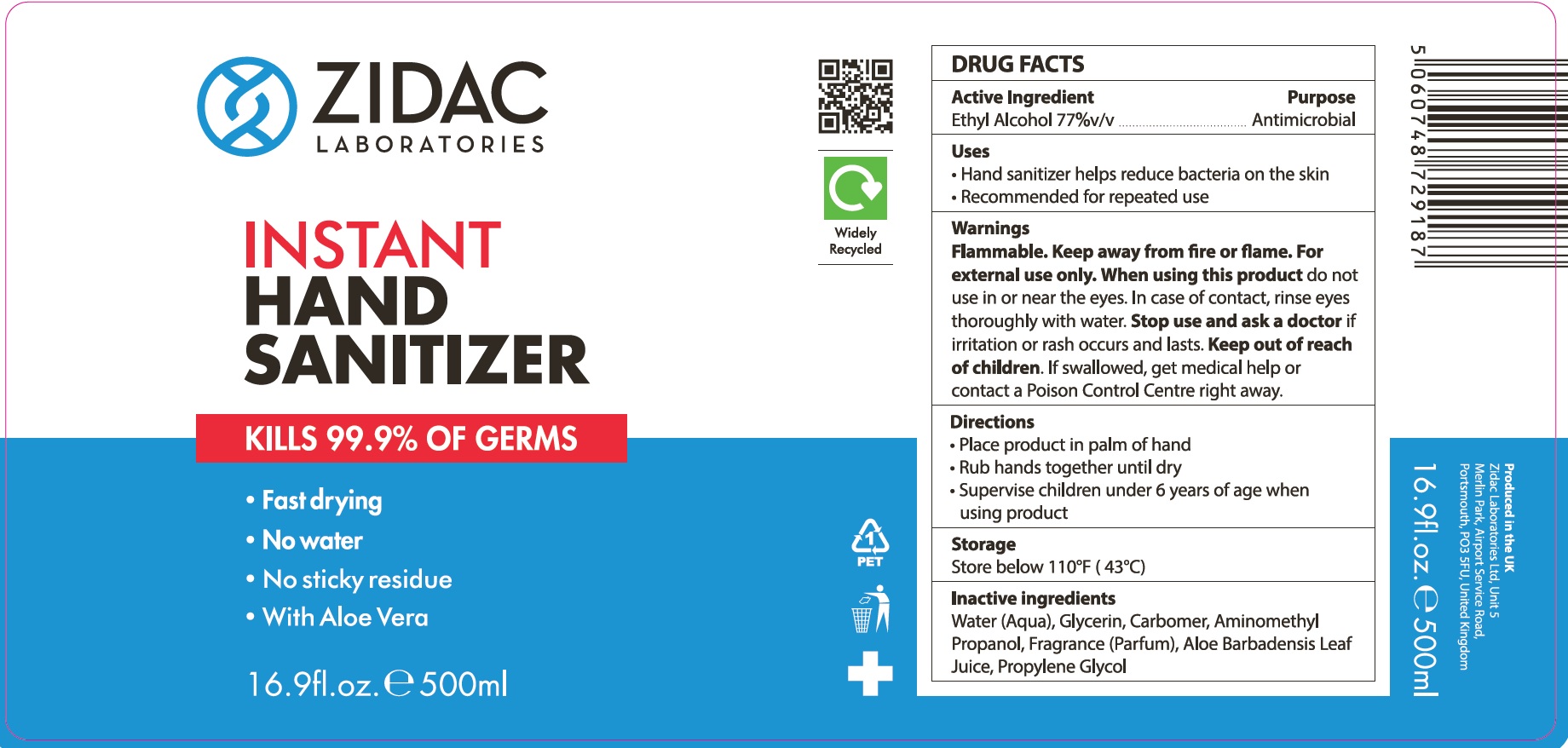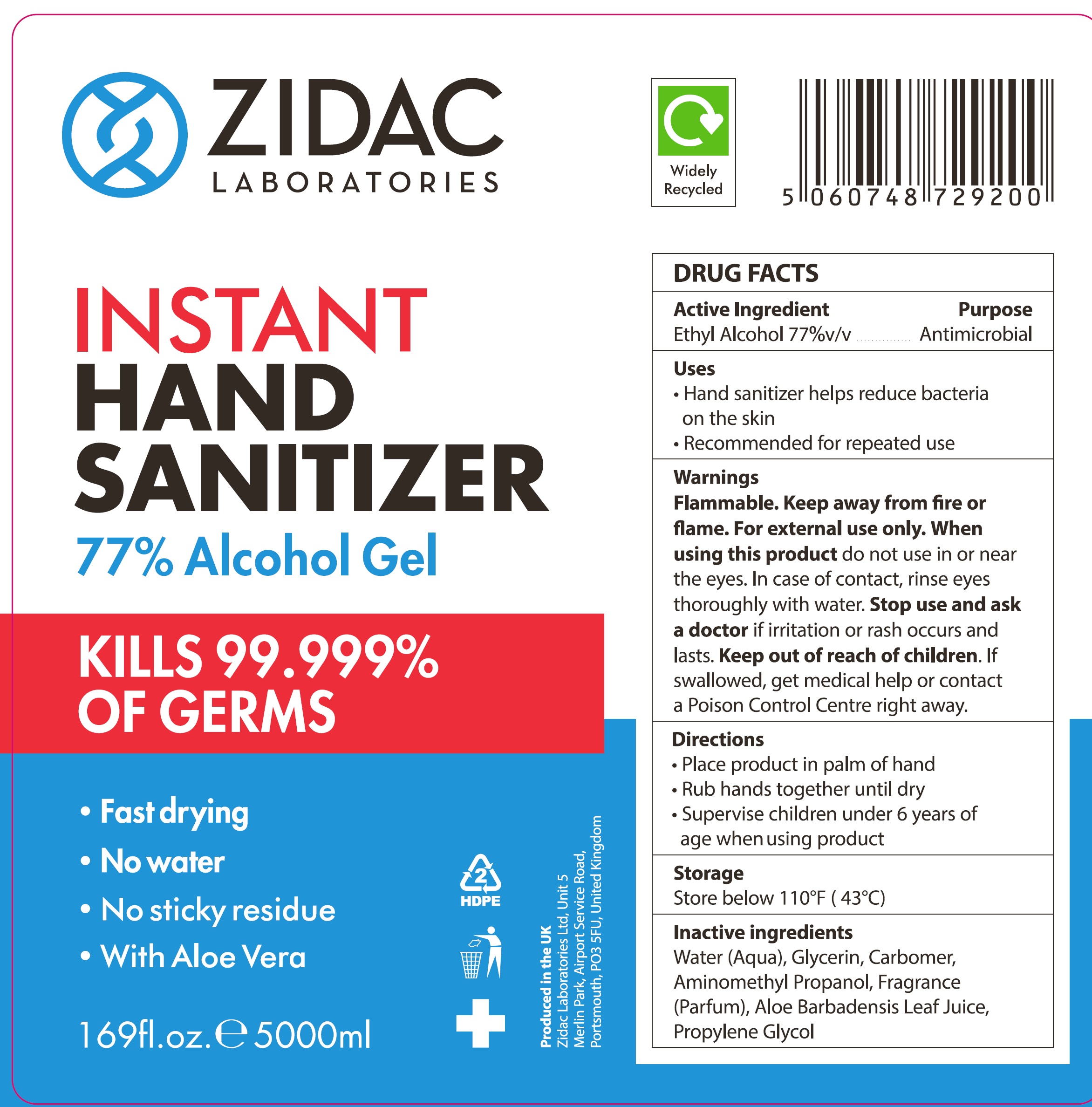 DRUG LABEL: Instant Hand Sanitizer
NDC: 79699-000 | Form: GEL
Manufacturer: Zidac Laboratories Ltd
Category: otc | Type: HUMAN OTC DRUG LABEL
Date: 20201002

ACTIVE INGREDIENTS: ALCOHOL 0.77 mL/1 mL
INACTIVE INGREDIENTS: WATER; GLYCERIN; CARBOMER HOMOPOLYMER, UNSPECIFIED TYPE; AMINOMETHYLPROPANOL; ALOE VERA LEAF; PROPYLENE GLYCOL

Instant Hand Sanitizer

Active Ingredient

Ethyl Alcohol 77%v/v

Purpose

Antimicrobial

Uses

- Hand sanitizer helps reduce bacteria on the skin
- Recommended for repeated use

Warnings

Flammable. Keep away from fire or flame. For external use only.

When using this product

do not use in or near the eyes. In case of contact, rinse eyes thoroughly with water.

Stop use and ask a doctor

if irritation or rash occurs and lasts.

Keep out of reach of children.

If swallowed, get medical help or contact a Poison Control Centre right away.

Directions

- Place product in palm of hand
- Rub hands together until dry
- Supervise children under 6 years of age when using product

Storage

Store below 110°F (43°C)

Inactive ingredients

Water (Aqua), Glycerin, Carbomer, Aminomethyl Propanol, Fragrance (Parfum), Aloe Barbadensis Leaf Juice, Propylene Glycol